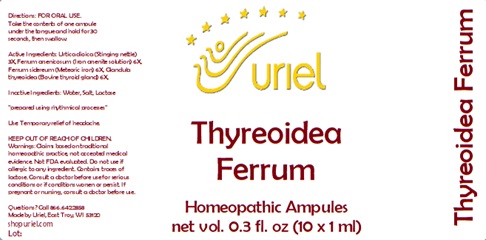 DRUG LABEL: Thyreoidea Ferrum
NDC: 48951-9378 | Form: LIQUID
Manufacturer: Uriel Pharmacy Inc.
Category: homeopathic | Type: HUMAN OTC DRUG LABEL
Date: 20240215

ACTIVE INGREDIENTS: URTICA DIOICA ROOT 3 [hp_X]/1 mL; THYROID, UNSPECIFIED 6 [hp_X]/1 mL; IRON 6 [hp_X]/1 mL; FERROUS ARSENATE 6 [hp_X]/1 mL
INACTIVE INGREDIENTS: LACTOSE, UNSPECIFIED FORM; WATER; SODIUM CHLORIDE

Thyreoidea Ferrum

INDICATIONS AND USAGE

Directions: FOR ORAL USE.

DOSAGE AND ADMINISTRATION

Take the contents of one ampule under the tongue and hold for 30 seconds, then swallow.

ACTIVE INGREDIENT

Active Ingredients: Urtica dioica (Stinging nettle) 3X, Ferrum arsenicosum (Iron arsenite solution) 6X, Ferrum sidereum (Meteoric iron) 6X, Glandula thyreoidea (Bovine thyroid gland) 6X,

Inactive Ingredients: Water, Salt, Lactose

"prepared using rhythmical processes"

PURPOSE

Use: Temporary relief of headache.

KEEP OUT OF REACH OF CHILDREN.

WARNINGS

Warnings: Claims based on traditional homeopathic practice, not accepted medical evidence. Not FDA evaluated. Do not use if allergic to any ingredient. Contains traces of lactose. Consult a doctor before use for serious conditions or if conditions worsen or persist. If pregnant or nursing, consult a doctor before use.

Questions? Call 866.642.2858
Made by Uriel, East Troy, WI 53120
shopuriel.com Lot: